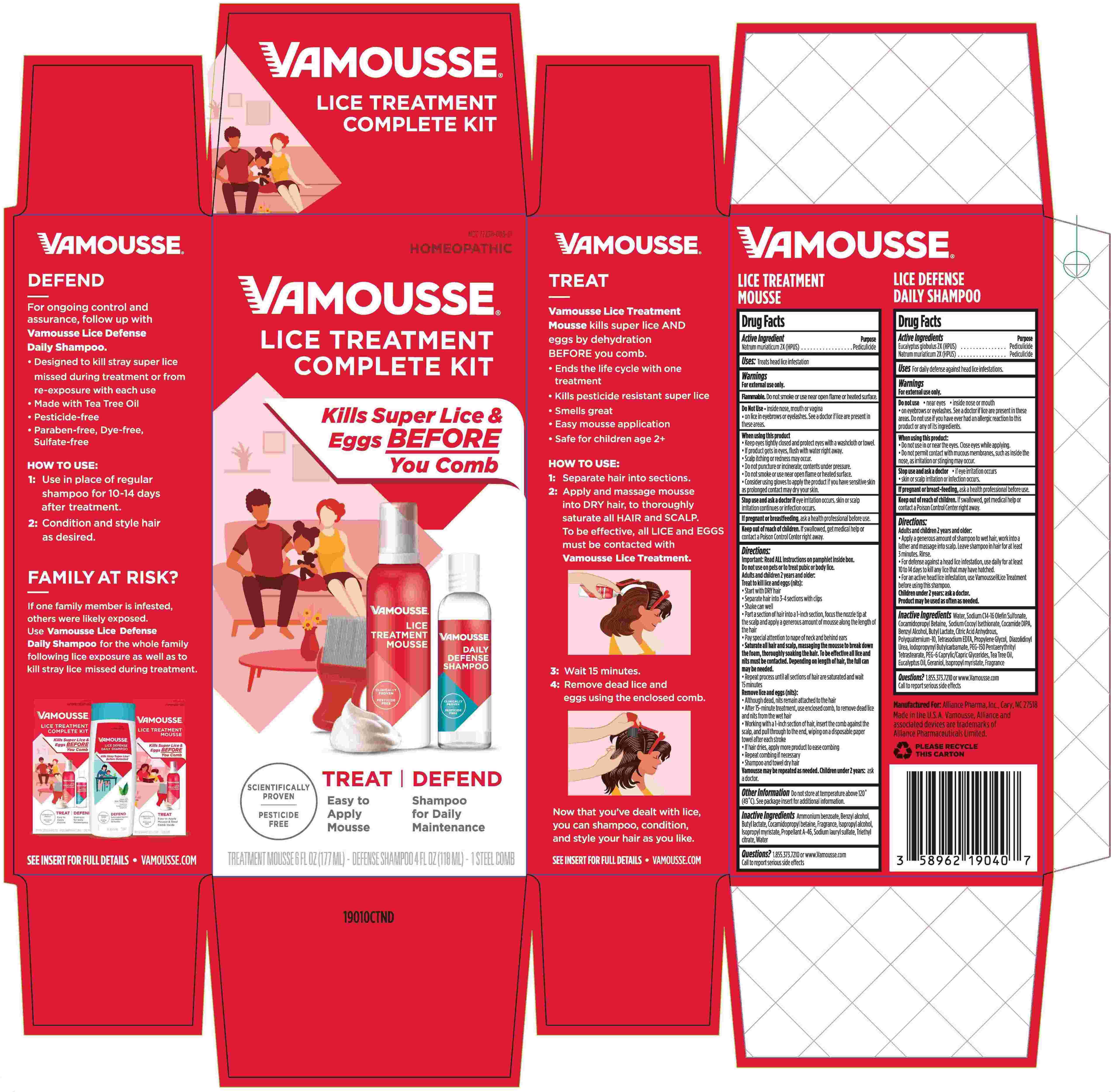 DRUG LABEL: Vamousse Lice Treatment Complete Kit
NDC: 72238-003 | Form: KIT | Route: TOPICAL
Manufacturer: Alliance Pharma Inc.
Category: homeopathic | Type: HUMAN OTC DRUG LABEL
Date: 20251205

ACTIVE INGREDIENTS: SODIUM CHLORIDE 2 [hp_X]/1 mL; EUCALYPTUS GLOBULUS LEAF 2 [hp_X]/1 mL; SODIUM CHLORIDE 2 [hp_X]/1 mL
INACTIVE INGREDIENTS: LIQUEFIED PETROLEUM GAS; ISOPROPYL ALCOHOL; GERANIOL; VANILLIN; TRIETHYL CITRATE; AMMONIUM BENZOATE; BUTYL LACTATE; SODIUM LAURYL SULFATE; BENZYL ALCOHOL; ISOPROPYL MYRISTATE; WATER; COCAMIDOPROPYL BETAINE; PEG-150 PENTAERYTHRITYL TETRASTEARATE; POLYQUATERNIUM-10 (125 MPA.S AT 2%); GERANIOL; SODIUM C14-16 OLEFIN SULFONATE; EUCALYPTUS OIL; EDETATE SODIUM; SODIUM COCOYL ISETHIONATE; COCAMIDOPROPYL BETAINE; CAPRYLOCAPROYL POLYOXYLGLYCERIDES 6; COCO DIISOPROPANOLAMIDE; TEA TREE OIL; BENZYL ALCOHOL; BUTYL LACTATE; ANHYDROUS CITRIC ACID; ISOPROPYL MYRISTATE; WATER; PROPYLENE GLYCOL; DIAZOLIDINYL UREA; IODOPROPYNYL BUTYLCARBAMATE

Vamousse Lice Treatment Kit

Active Ingredient

Natrum muriaticum 2X (HPUS)

Eucalyptus globulus 2X (HPUS)

Purpose

Pediculicide

Uses

Treats head lice infestation

WARNINGS

For external use only

Do Not Use inside nose, mouth, or vagina, on lice in eyebrows or eyelashes. See a doctor if lice are present in these areas.

When using this product Keep eyes tightly closed and protect eyes with a washcloth or towel.

If product gets in eyes, flush with water right away.

Scalp itching or redness may occur.

Do not puncture or incinerate, contents under pressure.

Do not smoke or use near open flame or heated surface.

Consider using gloves to apply the product if you have sensitive skin as prolonged contact may dry your skin.

Stop use and ask a doctor if eye irritation occurs, skin or scalp irritation continues or infection occurs.

PREGNANCY OR BREAST FEEDING

If pregnant or breastfeeding, ask a health professional before use.

Keep out of reach of children. If swallowed, get medical help or contact a Poison Control Center right away.

Directions

Directions Important: Read ALL instructions on pamphlet inside box.Do not use on pets or to treat pubic or body lice. Adults and children 2 years and older: Treat to kill lice and eggs (nits): Start off with DRY hair. Separate hair into 3-4 sections with clips. Shake can well. Part a section of hair into a 1-inch section, focus the nozzle tip on the scalp and apply a generous amount of mousse along the length of the hair. Pay special attention to nape of neck and behind ears. Saturate all hair and scalp, massaging the mousse to break down the foam, thoroughly soaking the hair. To be effective all lice and nits must be contacted. Depending on length of hair, the full can may be needed. Repeat process until all sections of hair are saturated and wait 15 minutes. Remove lice and eggs (nits): Although dead, nits remain attached to the hair. After 15-minute treatment, use enclosed comb, to remove dead lice and nits from wet hair. Working with a 1-inch section of hair, insert the comb against the scalp, and pull through to the end, wiping on a disposable paper towel after each stroke. If hair dries during combing, apply more product to ease combing. Repeat combing if necessary. Shampoo and towel dry hair. Vamousse may be repeated as needed. Children under 2 years: ask a doctor.

Other Information

Other Information Do not store at temperature above 120°F (49°C). See package insert for additional information.

INACTIVE INGREDIENT

Inactive Ingredients Ammonium benzoate, Benzyl alcohol, Butyl lactate, Cocomidopropyl betaine, Fragrance, Isopropyl alcohol, Isopropyl myristate, Propellant A-46, Sodium lauryl sulfate, Triethyl citrate, Water

QUESTIONS

Questions? 1.855.373.7210 or www.VamousseLice.com. Call to report serious side effects.